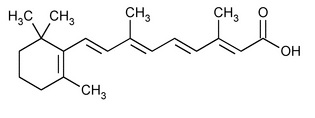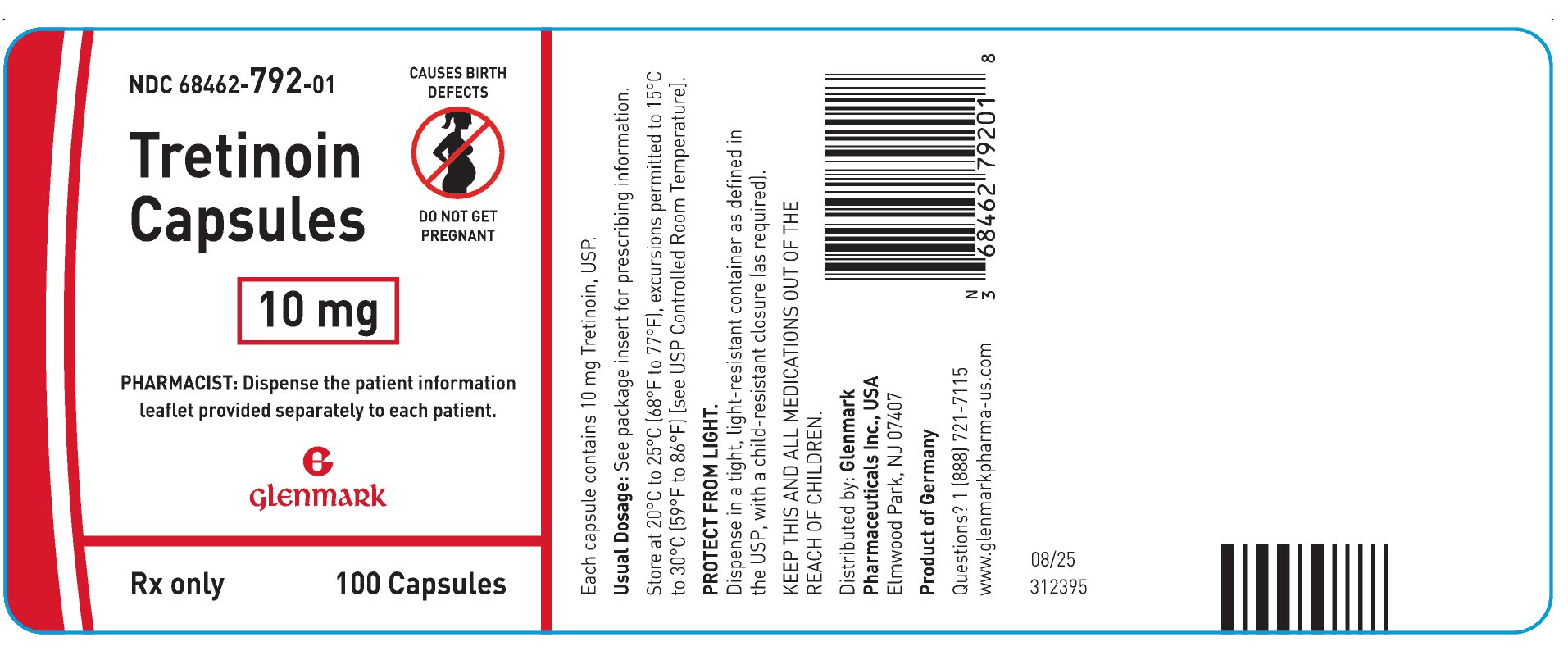 DRUG LABEL: Tretinoin
NDC: 68462-792 | Form: CAPSULE
Manufacturer: Glenmark Pharmaceuticals Inc., USA
Category: prescription | Type: HUMAN PRESCRIPTION DRUG LABEL
Date: 20260130

ACTIVE INGREDIENTS: TRETINOIN 10 mg/1 1
INACTIVE INGREDIENTS: BUTYLATED HYDROXYANISOLE; EDETATE DISODIUM; HYDROGENATED SOYBEAN OIL; SOYBEAN OIL; YELLOW WAX; GELATIN, UNSPECIFIED; GLYCERIN; SORBITOL; FERRIC OXIDE RED; TITANIUM DIOXIDE; AMMONIA; FERROSOFERRIC OXIDE; PROPYLENE GLYCOL; SHELLAC; SOYBEAN LECITHIN; MEDIUM-CHAIN TRIGLYCERIDES; OLEIC ACID; ASCORBYL PALMITATE; TOCOPHEROL; SUNFLOWER OIL

HIGHLIGHTS OF PRESCRIBING INFORMATION

These highlights do not include all the information needed to use TRETINOIN CAPSULES safely and effectively. See full prescribing information for TRETINOIN CAPSULES.
TRETINOIN capsules, for oral use
Initial U.S. Approval: 1995

WARNING: EMBRYO-FETAL TOXICITY and DIFFERENTIATION SYNDROME

See full prescribing information for complete boxed warning.

- Embryo-Fetal Toxicity: Tretinoin capsules can cause embryo-fetal loss and malformations when administered to a pregnant woman. Advise pregnant women of the potential risk to a fetus. Females of reproductive potential must have a negative pregnancy test before initiating tretinoin capsules. Advise females of reproductive potential to use two effective methods of contraception during treatment with tretinoin capsules and for 1 month after the last dose. Advise males with female partners of reproductive potential to use effective contraception during treatment with tretinoin capsules and for 1 week after the last dose. (5.1, 8.1, 8.3)
- Differentiation Syndrome, which can be life-threatening or fatal, occurred in about 26% of patients with APL who received tretinoin capsules. At first signs or symptoms of this syndrome, immediately initiate high-dose corticosteroid therapy and hemodynamic monitoring until resolution of signs and symptoms. Consider withholding tretinoin capsules for moderate and severe Differentiation Syndrome until resolution. (5.2)

1 INDICATIONS AND USAGE

Tretinoin capsules are a retinoid indicated for induction of remission in adults and pediatric patients 1 year of age and older with acute promyelocytic leukemia (APL), characterized by presence of t(15;17) translocation or presence of PML/RARα gene expression, and who are refractory to or who have relapsed from anthracycline chemotherapy or for whom anthracycline-based chemotherapy is contraindicated. (1)

2 DOSAGE AND ADMINISTRATION

- The recommended dosage of tretinoin capsules is 22.5 mg/m^2 orally twice daily until complete remission. (2.2)
- Discontinue 30 days after achievement of complete remission or after 90 days of treatment, whichever occurs first. (2.2)

3 DOSAGE FORMS AND STRENGTHS

Capsules: 10 mg (3)

4 CONTRAINDICATIONS

Hypersensitivity to tretinoin, any of its components, or other retinoids (4)

5 WARNINGS AND PRECAUTIONS

- Patients Without t(15;17) Translocation or PML/RARα Fusion: Tretinoin capsules may be initiated based on morphological diagnosis of APL. Confirm diagnosis by detection of the t(15;17) translocation or PML/RARα fusion. (5.3)
- Leukocytosis: Consider administering cytoreductive chemotherapy (including an anthracycline if not contraindicated or hydroxyurea) with tretinoin capsules in the setting of leukocytosis, as clinically indicated. (5.4)
- Intracranial Hypertension: Tretinoin capsules have been associated with benign intracranial hypertension, especially in pediatric patients. Consider interruption, dose reduction, or discontinuation of tretinoin capsules as appropriate. (5.5)
- Lipid Abnormalities: Patients experienced hypercholesterolemia and/or hypertriglyceridemia, which may be reversible upon completion of treatment. Monitor fasting triglycerides and cholesterol at baseline and periodically during treatment. (5.6)
- Hepatotoxicity: Monitor liver function test results at baseline and during treatment as clinically indicated. (5.7)
- Thromboembolic Events: Venous and arterial events have been reported; these events may occur during the first month of treatment with tretinoin capsules. (5.8, 7.4)

6 ADVERSE REACTIONS

The most common adverse reactions (≥30%) are headache, fever, skin/mucous membrane dryness, bone pain, malaise, shivering, upper respiratory tract disorders, dyspnea, hemorrhage, infections, nausea/vomiting, rash, peripheral edema, leukocytosis, pain, gastrointestinal hemorrhage, chest discomfort, abdominal pain (6.1).

To report SUSPECTED ADVERSE REACTIONS, contact Glenmark Pharmaceuticals Inc., USA at 1 (888) 721-7115 or FDA at 1-800-FDA-1088 or www.fda.gov/medwatch.

7 DRUG INTERACTIONS

- Strong CYP3A Inhibitors and Inducers: Avoid coadministration with strong CYP3A inhibitors and inducers. (7.1)
- Concomitant Use of Products Known to Cause Intracranial Hypertension: Avoid concomitant use with other products that can cause intracranial hypertension. (7.2)
- Vitamin A: Avoid concomitant use with vitamin A. (7.3)
- Anti-fibrinolytic Agents: Avoid concomitant use with anti-fibrinolytic agents. (7.4)

8 USE IN SPECIFIC POPULATIONS

Lactation: Advise not to breastfeed. (8.2)

FULL PRESCRIBING INFORMATION

WARNING: EMBRYO-FETAL TOXICITY and DIFFERENTIATION SYNDROME

- Tretinoin capsules can cause embryo-fetal loss and malformations when administered to a pregnant woman. Advise pregnant women of the potential risk to a fetus. Females of reproductive potential must have a negative pregnancy test before initiating tretinoin capsules. Advise females of reproductive potential to use two effective methods of contraception during treatment with tretinoin capsules and for 1 month after the last dose. Advise males with female partners of reproductive potential to use effective contraception during treatment with tretinoin capsules and for 1 week after the last dose [see Warnings and Precautions (5.1), Use in Specific Populations (8.1, 8.3)].
- Differentiation Syndrome, which can be life-threatening or fatal, occurred in about 26% of patients with APL who received tretinoin capsules. At first signs or symptoms of this syndrome, immediately initiate high-dose corticosteroid therapy and hemodynamic monitoring until resolution of signs and symptoms. Consider withholding tretinoin capsules for moderate and severe Differentiation Syndrome until resolution [see Warnings and Precautions (5.2)].

1 INDICATIONS AND USAGE

Tretinoin capsules are indicated for the induction of remission in adults and pediatric patients 1 year of age and older with acute promyelocytic leukemia (APL) characterized by the presence of the t(15;17) translocation or PML/RARα gene expression, and who are refractory to or who have relapsed from anthracycline chemotherapy or for whom anthracycline-based chemotherapy is contraindicated.

2 DOSAGE AND ADMINISTRATION

2.1 Important Safety Information

Verify pregnancy status in females of reproductive potential prior to initiating tretinoin capsules. Females of reproductive potential must have a negative pregnancy test before initiating tretinoin capsules [see Use in Specific Populations (8.3)].

2.2 Recommended Dosage

The recommended dosage of tretinoin capsules is 22.5 mg/m^2 orally twice daily until complete remission is documented. Discontinue tretinoin capsules 30 days after achievement of complete remission or after 90 days of treatment, whichever occurs first.

Discontinue tretinoin capsules if the t(15;17) translocation or PML/RARα fusion has not been identified [see Warnings and Precautions (5.3)]. Take tretinoin capsules with a meal. Swallow tretinoin capsules whole with water. Do not chew, dissolve, or open capsule.

Do not take a missed dose of tretinoin capsules unless it is more than 10 hours until the next scheduled dose. If vomiting occurs after tretinoin capsules administration, do not take an additional dose, but continue with the next scheduled dose.

3 DOSAGE FORMS AND STRENGTHS

Tretinoin Capsules are available as:

10 mg: Pink, oval, soft-gelatin capsules printed with black ‘T 10’ filled with yellow to orange, opaque, viscous suspension.

4 CONTRAINDICATIONS

Tretinoin capsules are contraindicated in patients with a known hypersensitivity to tretinoin capsules, any of its components, or other retinoids. Reactions have included rash, pruritus, face edema, and dyspnea. [see Adverse Reactions (6.1)].

5 WARNINGS AND PRECAUTIONS

5.1 Embryo-Fetal Toxicity

Tretinoin capsules can cause embryo-fetal loss and malformations when administered to a pregnant woman. Tretinoin capsules are a retinoid and there is an increased risk of major congenital malformations, spontaneous abortions and premature births following exposure to retinoids during pregnancy in humans. Tretinoin has teratogenic and embryotoxic effects in mice, rats, hamsters, rabbits and pigtail monkeys at doses less than the human dose on a mg/m^2 basis.

Advise pregnant women of the potential risk to a fetus. Advise females of reproductive potential to use 2 effective methods of contraception during treatment with tretinoin capsules and for 1 month following the last dose. Advise males with female partners of reproductive potential to use effective contraception during treatment with tretinoin capsules and for 1 week following the last dose [see Use in Specific Populations (8.1, 8.3)].

5.2 Differentiation Syndrome

Differentiation Syndrome, which may be life-threatening or fatal, occurred in about 26% of patients with APL who received tretinoin capsules [see Adverse Reactions (6.1)]. Symptoms include fever, dyspnea, acute respiratory distress, weight gain, radiographic pulmonary infiltrates, pleural and pericardial effusions, edema, and hepatic, renal, and multi-organ failure. This syndrome has been accompanied by impaired myocardial contractility and episodic hypotension and it has been observed with or without concomitant leukocytosis. This syndrome generally occurs during the first month of treatment, as early as following the first dose. Endotracheal intubation and mechanical ventilation were required in some cases due to progressive hypoxemia and several patients have died with multi-organ failure.

At the first signs or symptoms of this syndrome, immediately administer dexamethasone 10 mg intravenously every 12 hours until signs and symptoms have abated for at least 3 days and initiate hemodynamic monitoring until resolution of signs and symptoms. Consider withholding tretinoin capsules for moderate and severe differentiation syndrome until resolution [see Adverse Reactions (6.1)].

5.3 Patients Without t(15;17) Translocation or PML/RARα Fusion

Tretinoin capsules may be initiated based on the morphological diagnosis of acute promyelocytic leukemia (APL). Confirm the diagnosis of APL by detection of the t(15;17) translocation using cytogenetic studies or PML/RARα fusion using molecular diagnostic techniques. Tretinoin capsules are not recommended for use in patients without these genetic markers [see Indications and Usage (1)].

5.4 Leukocytosis

Rapidly evolving leukocytosis, which can be life-threatening, occurred in about 40% of patients with APL who received tretinoin capsules [see Adverse Reactions (6.1)]. Patients who present with a baseline white blood cell count (WBC) > 5 × 10^9/L have an increased risk. Patients who receive chemotherapy with tretinoin capsules may be at a reduced risk. Rapidly evolving leukocytosis is associated with a higher risk of life-threatening complications.

Consider administering cytoreductive chemotherapy (including an anthracycline if not contraindicated or hydroxyurea) with tretinoin capsules in the setting of leukocytosis, as clinically indicated.

5.5 Intracranial Hypertension

Retinoids, including tretinoin capsules, have been associated with intracranial hypertension, especially in pediatric patients. Early signs and symptoms include papilledema, headache, nausea, vomiting, and visual disturbances. Evaluate patients with these symptoms for intracranial hypertension, and, if present, institute appropriate care in concert with neurological assessment. Consider interruption, dose reduction, or discontinuation of tretinoin capsules as appropriate.

The concomitant use of other products (e.g., tetracyclines) that can cause intracranial hypertension may increase the risk. Avoid concomitant use of tretinoin capsules with other products that can cause intracranial hypertension [see Drug Interactions (7.2)].

5.6 Lipid Abnormalities

Hypercholesterolemia and/or hypertriglyceridemia has occurred in up to 60% of patients who received tretinoin capsules. These changes may be reversible upon completion of treatment. The clinical consequences of increased triglycerides and cholesterol are unknown, but venous thrombosis and myocardial infarction have been reported in patients who ordinarily are at low risk for such complications.

Monitor fasting triglycerides and cholesterol at baseline and periodically during treatment.

5.7 Hepatotoxicity

Elevated liver function test results occurred in 50% to 60% of patients during treatment with tretinoin capsules. Most of these abnormalities resolved without interruption of tretinoin capsules or after completion of treatment.

Monitor liver function test at baseline and during treatment as clinically indicated. Consider withholding tretinoin capsules if liver function test results increase to greater than 5 times the upper limit of normal values until resolution.

5.8 Thromboembolic Events

Venous and arterial thromboembolic events, including cerebrovascular accident, myocardial infarction and renal infarct have been reported with tretinoin capsules [see Adverse Reactions (6.2)]. These events may occur during the first month of treatment. Patients taking anti-fibrinolytic agents may have an increased risk.

Avoid concomitant use of tretinoin capsules and anti-fibrinolytic agents, such as tranexamic acid, aminocaproic acid or aprotinin [see Drug Interactions (7.4)].

6 ADVERSE REACTIONS

The following clinically significant adverse reactions are described elsewhere in the labeling:

- Differentiation Syndrome [see Warnings and Precautions (5.2)]
- Leukocytosis [see Warnings and Precautions (5.4)]
- Intracranial hypertension [see Warnings and Precautions (5.5)]
- Lipid abnormalities [see Warnings and Precautions (5.6)]
- Hepatotoxicity [see Warnings and Precautions (5.7)]
- Thromboembolic events [see Warnings and Precautions (5.8)]

6.1 Clinical Trials Experience

Because clinical trials are conducted under widely varying conditions, adverse reaction rates observed in the clinical trials of a drug cannot be directly compared to rates in the clinical trials of another drug and may not reflect the rates observed in practice.

Acute Promyelocytic Leukemia

The safety of tretinoin capsules was evaluated in patients with APL who received tretinoin capsules at a dose of 22.5 mg/m^2 orally twice daily [see Clinical Studies (14)].

The most common adverse reactions (≥30%) were headache, fever, skin/mucous membrane dryness, bone pain, malaise, shivering, upper respiratory tract disorders, dyspnea, hemorrhage, infections, nausea/vomiting, rash, peripheral edema, leukocytosis, pain, gastrointestinal hemorrhage, chest discomfort, abdominal pain.

Table 1 summarizes the adverse reactions for patients with APL.

Table 1. Adverse Reactions (≥ 10%) Occurring in Patients with APL Who Received Tretinoin Capsules

Adverse Reaction | Tretinoin Capsules
Adverse Reaction | All Grades (%)
Nervous system disorders
Headache | 86
Dizziness | 20
Paresthesias | 17
Anxiety | 17
Insomnia | 14
Depression | 14
Confusion | 11
General disorders
Fever | 83
Skin/mucous membrane dryness | 77
Malaise | 66
Shivering | 63
Peripheral edema | 52
Pain | 37
Chest discomfort | 32
Edema | 29
Mucositis | 26
Weight increase | 23
Anorexia | 17
Weight decrease | 17
Musculoskeletal and connective tissue disorders
Bone pain | 77
Myalgia | 14
Respiratory, thoracic and mediastinal disorders
Upper respiratory tract disorders | 63
Dyspnea | 60
Respiratory insufficiency | 26
Pleural effusion | 20
Rales | 14
Expiratory wheezing | 14
Pneumonia | 14
Vascular disorders
Hemorrhage | 60
Gastrointestinal hemorrhage | 34
Flushing | 23
Hypotension | 14
Hypertension | 11
Phlebitis | 11
Infections and infestations
Infections | 58
Gastrointestinal disorders
Nausea/vomiting | 57
Abdominal pain | 31
Other gastrointestinal disorders | 26
Diarrhea | 23
Constipation | 17
Dyspepsia | 14
Abdominal distention | 11
Skin and subcutaneous tissue disorders
Rash | 54
Pruritus | 20
Increased sweating | 20
Alopecia | 14
Skin changes | 14
Blood and lymphatic system disorders
Leukocytosis | 49
Differentiation syndrome^1 | 26
Disseminated intravascular coagulation | 26
Ear and labyrinth disorders
Earache or feeling of fullness in the ears | 23
Cardiac disorders
Arrhythmias | 23
Eye disorders
Visual disturbances | 17
Ocular disorders | 17
Renal and urinary disorders
Renal insufficiency | 11

^1Differentiation syndrome can be associated with other commonly reported events such as fever, leukocytosis, dyspnea, pneumonia, pleural effusion, pericardial effusion, hypotension, edema, weight gain, and renal failure.

Adverse reactions that occurred in <10% of patients who received tretinoin capsules include:

- Hepatobiliary disorders: Hepatosplenomegaly (9%), hepatitis (3%), unspecified liver disorder (3%).
- Musculoskeletal and connective tissue disorders: Flank pain (9%), bone inflammation (3%).
- Nervous system disorders: Agitation (9%), cerebral hemorrhage (9%), intracranial hypertension (9%), hallucination (6%), abnormal gait, agnosia, aphasia, asterixis, cerebellar edema, cerebellar disorders, convulsions, coma, CNS depression, dysarthria, encephalopathy, facial paralysis, hemiplegia, hyporeflexia, hypotaxia, no light reflex, neurologic reaction, spinal cord disorder, stroke, tremor, leg weakness, unconsciousness, dementia, forgetfulness, somnolence, and slow speech (3% each).
- Renal and urinary disorders: Dysuria (9%), acute renal failure, micturition frequency, renal tubular necrosis, and enlarged prostate (3% each).
- Respiratory, thoracic and mediastinal disorders: Lower respiratory tract disorders (9%), pulmonary infiltration (6%), bronchial asthma, pulmonary edema, larynx edema, and unspecified pulmonary disease (3% each).
- Infections and infestations: Cellulitis (8%).
- Blood and lymphatic system disorders: Lymph disorders (6%).
- Cardiovascular disorders: Cardiac failure (6%), cardiac arrest, myocardial infarction, enlarged heart, heart murmur, myocarditis, pericarditis, and secondary cardiomyopathy (3% each).
- Ear and labyrinth disorders: Hearing loss and other unspecified auricular disorders (6%), irreversible hearing loss (<1%).
- General disorders: Face edema (6%), pallor (6%), hypothermia (3%).
- Metabolism and nutrition disorders: Fluid imbalance (6%), acidosis (3%).
- Eye disorders: Changed visual acuity (6%), visual field defects (3%).
- Gastrointestinal disorders: Ascites, ulcer (3% each).
- Vascular disorders: Ischemia and pulmonary hypertension (3% each).

6.2 Postmarketing Experience

Because these reactions are reported voluntarily from a population of uncertain size, it is not always possible to reliably estimate their frequency or establish a causal relationship to drug exposure.

Erythema nodosum, basophilia and hyperhistaminemia, Sweet’s Syndrome, organomegaly, hypercalcemia, pancreatitis, myositis, thrombosis (both venous and arterial), thrombocytosis, genital ulceration and vasculitis, predominantly involving the skin.

7 DRUG INTERACTIONS

7.1 Effects of Other Drugs on Tretinoin Capsules

Strong or moderate CYP3A Inhibitors

Avoid concomitant use of tretinoin capsules with strong CYP3A inhibitors if possible and monitor more frequently if concomitant use is unavoidable. Monitor patients taking moderate CYP3A inhibitors concomitantly with tretinoin capsules more frequently for adverse reactions.

Tretinoin is a CYP3A substrate. Concomitant use with a strong CYP3A4 inhibitor increases tretinoin plasma concentrations, which may increase the risk of adverse reactions [see Clinical Pharmacology (12.3)].

Strong CYP3A Inducers

Concomitant use of tretinoin capsules with strong CYP3A4 inducers may decrease tretinoin plasma concentrations, which may reduce its efficacy. Avoid concomitant use with strong CYP3A inducers if possible.

7.2 Concomitant Use of Products Known to Cause Intracranial Hypertension

Intracranial hypertension has been reported in patients who received tretinoin capsules and concomitant use of other products that can cause intracranial hypertension, such as tetracyclines, may increase the risk. Avoid concomitant use of tretinoin capsules with other products agents that can cause intracranial hypertension [see Warnings and Precautions (5.5)].

7.3 Vitamin A

The concomitant use of vitamin A with tretinoin capsules may lead to vitamin A related adverse reactions. Avoid concomitant use of tretinoin capsules with vitamin A.

7.4 Anti-fibrinolytic Agents

Fatal thrombotic complications have been reported in patients who have received tretinoin capsules and concomitant use of anti-fibrinolytic agents may increase the risk. Avoid concomitant use of tretinoin capsules with anti-fibrinolytic agents [see Warnings and Precautions (5.8)].

8 USE IN SPECIFIC POPULATIONS

8.1 Pregnancy

Risk Summary

Based on findings in animals and its mechanism of action [see Clinical Pharmacology (12.1)], tretinoin capsules can cause embryo-fetal loss and malformations when administered to a pregnant woman. Tretinoin capsules are a retinoid and there is an increased risk of major congenital malformations, spontaneous abortions and premature births following exposure to retinoids during pregnancy in humans. Tretinoin was teratogenic and embryotoxic in mice, rats, hamsters, rabbits and pigtail monkeys at doses less than the human dose on a mg/m^2 basis (see Data). Advise pregnant women of the potential risk to a fetus.

The estimated background risk of major birth defects and miscarriage for the indicated population(s) is unknown. All pregnancies have a background risk of birth defect, loss, or other adverse outcomes. In the U.S. general population, the estimated background risk of major birth defects and miscarriage in clinically recognized pregnancies is 2% to 4% and 15% to 20%, respectively.

Data

Human Data

Tretinoin capsules are a retinoid and increased spontaneous abortions and major fetal abnormalities related to the use of retinoids have been documented in humans. Reported malformations include abnormalities of the central nervous system, musculoskeletal system, external ear, eye, thymus and great vessels; and facial dysmorphia, cleft palate, and parathyroid hormone deficiency. Some of these abnormalities were fatal.

IQ scores less than 85, with or without obvious CNS abnormalities, have been reported in pediatrics exposed to retinoids in utero.

Animal Data

Tretinoin causes fetal resorptions and a decrease in live fetuses in all animals studied. Gross external, soft tissue and skeletal alterations occurred at doses higher than 0.7 mg/kg/day in mice, 2 mg/kg/day in rats, 7 mg/kg/day in hamsters, and at a dose of 10 mg/kg/day, the only dose tested, in pigtail monkeys (about 1/20, 1/4, and 1/2 and 4 times the human dose, respectively, on a mg/m^2 basis).

8.2 Lactation

There are no data on the presence of tretinoin in human milk, the effects on the breastfeed child or the effects on milk production. Because of the potential for serious adverse reactions from tretinoin in breastfed infants, advise women not to breastfed during treatment with tretinoin capsules and for 1 week after the last dose.

8.3 Use in Females and Males of Reproductive Potential

Tretinoin capsules can cause embryo-fetal loss and malformations when administered to a pregnant woman [see Use in Specific Populations (8.1)].

Pregnancy Testing

Verify pregnancy status in females of reproductive potential prior to initiating tretinoin capsules. Females of reproductive potential must have a negative pregnancy test within 1 week prior to initiating tretinoin capsules with a sensitivity of at least 50 mIU/mL.

Contraception

Females

Advise females of reproductive potential to abstain continuously from sexual intercourse or to use two effective methods of contraception. Counsel patients to use two effective methods of contraception during treatment with tretinoin capsules and for 1 month after the last dose. Two methods of effective contraception is indicated even where there has been a history of infertility, unless due to hysterectomy. Refer females of reproductive potential to a qualified provider of contraceptive methods, if needed.

Males

Advise males with female partners of reproductive potential to use effective contraception during and after treatment with tretinoin capsules and for 1 week after the last dose.

Infertility

Males

Based on testicular toxicities observed in dogs, tretinoin capsules may impair male fertility [see Nonclinical Toxicology (13.1)]. The reversibility of effect on fertility is unknown.

8.4 Pediatric Use

Safety and effectiveness of tretinoin capsules has been established in pediatric patients 1 year of age and older and the information on this use is discussed throughout the labeling. The maximum tolerated dose is lower in pediatric patients compared to adults. Some pediatric patients experience severe headache and intracranial hypertension, which required management with an analgesic and a lumbar puncture. Dose reduction may be considered for pediatric patients experiencing serious and/or intolerable adverse reactions.

Safety and effectiveness in pediatric patients less than 1 year of age have not been established.

8.5 Geriatric Use

Across clinical studies of tretinoin capsules, 21% were 60 years and older. No overall differences in safety or effectiveness were observed between these patients and younger patients.

10 OVERDOSAGE

In case of overdose with tretinoin capsules, reversible signs of hypervitaminosis A (headache, nausea, vomiting, mucocutaneous symptoms) can appear. Overdosage with other retinoids has been associated with transient headache, facial flushing, cheilosis, abdominal pain, dizziness and ataxia. These symptoms have quickly resolved without apparent residual effects.

There is no specific treatment in the case of an overdose; however, it is important that the patient be treated in a special hematological unit.

11 DESCRIPTION

Tretinoin, USP is a retinoid. The chemical name is all-trans retinoic acid. The molecular formula is C20H28O2 and the molecular weight is 300.44 g/mol. The structural formula is:

It is a yellow to yellow-orange, crystalline powder with melting point at about 182°C (with decomposition). Tretinoin, USP is very sparingly soluble in water.

Tretinoin is available as capsules containing 10 mg tretinoin for oral use. Each capsule contains the following inactive ingredients: butylated hydroxyanisole, edetate disodium, hydrogenated vegetable oil, refined soybean oil and yellow wax. The ingredients in the capsule shell include gelatin, glycerin, sorbitol, red iron oxide, titanium dioxide. The ingredients in the edible imprinting ink include ammonium hydroxide, black iron oxide, propylene glycol and shellac. The ingredients in the processing aid Phosal 53 include lecithin, caprylic/capric triglycerides, ethanol, sunflower mono/diglycerides, oleic acid, ascorbyl palmitate and tocopherol.

12 CLINICAL PHARMACOLOGY

12.1 Mechanism of Action

Tretinoin induces cytodifferentiation and decreased proliferation of APL cells in culture and in vivo. In APL patients, tretinoin treatment produces an initial maturation of the primitive promyelocytes derived from the leukemic clone, followed by a repopulation of the bone marrow and peripheral blood by normal, polyclonal hematopoietic cells in patients achieving complete remission (CR). The exact mechanism of action of tretinoin in APL is unknown.

12.2 Pharmacodynamics

The exposure-response relationship and time course of pharmacodynamic response for the safety and effectiveness of tretinoin capsules have not been characterized.

12.3 Pharmacokinetics

Following the administration of tretinoin capsules 22.5 mg/m^2 orally twice daily, the mean ± SD peak tretinoin concentrations after the first dose was 394 ± 89 and after 1 week of continuous treatment was 138 ± 139 ng/mL, while area under the curve (AUC) after the first dose was 537 ± 191 ng·h/mL and after 1 week of continuous treatment was 249 ± 185 ng·h/mL.

Absorption

Time to reach peak concentration was between 1 and 2 hours. The absolute bioavailability of tretinoin capsules was approximately 50%.

Effect of Food

The effect of food on the absorption of tretinoin capsules has not been characterized. Food increases the absorption of retinoids, as a class.

Distribution

The apparent volume of distribution of tretinoin has not been determined. Protein binding is greater than 95%, predominately to albumin. Plasma protein binding remains constant over the concentration range of 10 to 500 ng/mL.

Elimination

The terminal elimination half-life of tretinoin following initial dosing is 0.5 to 2 hours in patients with APL.

Metabolism

Tretinoin induced its own metabolism with plasma concentrations after 1 week of continuous therapy decreased to one-third of their day 1 values. Tretinoin is metabolized by cytochrome P450 enzymes, CYP3A4, 2C8, and 2E and undergoes glucuronidation by UGT2B7. Metabolites include 9-cis retinoic acid, 13-cis retinoic acid, 4-oxo trans retinoic acid, 4-oxo cis retinoic acid, and 4-oxo trans retinoic acid glucuronide. The metabolites 4-oxo retinoic acid and 4-oxo trans retinoic acid glucuronide have one-third of the pharmacological activity of the parent compound.

Excretion

Following administration of radiolabeled tretinoin 2.75 mg and 50 mg (0.53 to 9.6 times the approved recommended dosage based on 1.7 m^2), approximately 63% of radioactivity was recovered in the urine within 72 hours and 31% appeared in the feces within 6 days.

Specific Populations

The effect of age, sex, race, renal impairment, and hepatic impairment on the pharmacokinetics of tretinoin is unknown.

Drug Interaction Studies

Clinical Studies and Post Marketing Experience

Strong CYP3A inhibitors: Tretinoin AUC increased by 72% following concomitant use with ketoconazole (strong CYP3A inhibitor). Increased tretinoin toxicity has also been reported post-marketing with strong CYP3A inhibitors including certain antimycotics.

Moderate CYP3A Inhibitors: Increased tretinoin toxicity following concomitant use of tretinoin capsules with certain antimycotics that are moderate CYP3A4 inhibitors has been reported post-marketing.

In Vitro Studies

Effect of Tretinoin on Transporters: Tretinoin does not inhibit P-gp and BCRP in vitro.

13 NONCLINICAL TOXICOLOGY

13.1 Carcinogenesis, Mutagenesis, Impairment of Fertility

No 2-year carcinogenicity studies in rodents have been conducted with tretinoin. In a carcinogenicity study, female B5D2F1 mice pretreated with a carcinogen diethylnitrosamine (DEN, intraperitoneal 50 mg/kg and 100 mg/kg) received dietary supplement of all-trans-retinoic acid (tretinoin) for 12 months. Tretinoin at a dose of 30 mg/kg/day in the diet (about 2 times the human dose on a mg/m^2 basis) was shown to increase the rate of DEN-induced mouse hepatocellular carcinomas. Tretinoin in combination with 50 mg/kg of DEN also increased the incidence of hemangiomas and hemangiosarcomas.

Tretinoin was negative when tested in the Ames and Chinese hamster V79 cell HGPRT assays for mutagenicity. A 2-fold increase in the sister chromatid exchange (SCE) has been demonstrated in human diploid fibroblasts, but other chromosome aberration assays, including an in vitro assay in human peripheral lymphocytes and an in vivo mouse micronucleus assay, did not show a clastogenic or aneuploidogenic effect.

Adverse effects on fertility and reproductive performance were not observed in studies conducted in rats at doses up to 5 mg/kg/day (about 2/3 the human dose on a mg/m^2 basis). In a 6-week toxicology study in dogs, testicular degeneration, with increased numbers of immature spermatozoa, were observed at 10 mg/kg/day (about 4 times the equivalent human dose in mg/m^2).

14 CLINICAL STUDIES

The efficacy of tretinoin capsules has been evaluated in 114 previously treated patients and in 67 previously untreated (“de novo”) patients with APL in one open-label, uncontrolled single investigator clinical study (Memorial Sloan-Kettering Cancer Center [MSKCC]) and in two cohorts of compassionate cases treated by multiple investigators under the auspices of the National Cancer Institute (NCI). Patients received tretinoin capsules 22.5 mg/m^2 orally twice daily for up to 90 days following the first dose or 30 days following achievement of complete remission. Efficacy results are shown Table 2.

Table 2. Efficacy Results in a Controlled Clinical Trial (MSKCC) and Compassionate Use

 | MSKCC |  | NCI Cohort 1 |  | NCI Cohort 2
 | Relapsed n=20 | De Novo n=15 | Relapsed* n=48 | De Novo n=14 | Relapsed n=46 | De Novo† n=38
Complete Remission | 16 (80%) | 11 (73%) | 24 (50%) | 5 (36%) | 24 (52%) | 26 (68%)
Median Survival (months) | 10.8 | NR | 5.8 | 0.5 | 8.8 | NR
Median Follow-up (months) | 9.9 | 42.9 | 5.6 | 1.2 | 8.0 | 13.1
NR = Not Reached
NA = Not Available
* Including 9 chemorefractory patients
† Including 8 patients who received chemotherapy but failed to enter remission

The median time to complete remission was between 40 and 50 days (range: 2 to 120 days). Most patients received cytotoxic chemotherapy during the remission phase.

Ten of 15 pediatric cases achieved complete remission (8 of 10 males and 2 of 5 females).

16 HOW SUPPLIED/STORAGE AND HANDLING

Tretinoin Capsules are available as:

10 mg: | Pink, oval, soft-gelatin capsule printed with black ‘T 10’ filled with yellow to orange, opaque, viscous suspension.

NDC 68462-792-01 Bottle of 100 capsules with child-resistant closure

Store at 20°C to 25°C (68° F to 77°F); excursions permitted to 15°C to 30°C (59° F to 86°F) [see USP Controlled Room Temperature].

Keep bottle tightly closed. Protect from light.

17 PATIENT COUNSELING INFORMATION

Embryo-Fetal Toxicity

Advise female patients of the potential risk to a fetus. Advise females of reproductive potential to inform their healthcare provider of a known or suspected pregnancy [see Warnings and Precautions (5.1) and Use in Specific Populations (8.1, 8.3)].

Advise females of reproductive potential to use 2 methods of effective contraception during treatment with tretinoin capsules and for 1 month after the last dose [see Use in Specific Populations (8.3)].

Advise males with female partners of reproductive potential to use effective contraception during treatment with tretinoin capsules and for 1 week after the last dose [see Use in Specific Populations (8.3)].

Differentiation Syndrome

Advise patients that tretinoin capsules can cause differentiation syndrome. Ask patients to immediately report any symptoms suggestive of differentiation syndrome, such as fever, cough or difficulty breathing, decreased urinary output, low blood pressure, rapid weight gain, or swelling of their arms or legs, to their healthcare provider for further evaluation [see Warnings and Precautions (5.2)].

Patients Without t(15;17) Translocation or PML/RARα Fusion

Advise patients that tretinoin capsules are not recommended for use in patients without t(15;17) translocation or PML/RARα fusion [see Warnings and Precautions (5.3)].

Leukocytosis

Inform patients that rapidly evolving leukocytosis, which can be life-threatening, can occur during treatment with tretinoin capsules [see Warnings and Precautions (5.4)].

Intracranial Hypertension

Advise patients that tretinoin capsules can cause intracranial hypertension, especially in pediatric patients. Ask patients to immediately report any symptoms suggestive of intracranial hypertension, such as headache, nausea, vomiting, and visual disturbances [see Warnings and Precautions (5.5)].

Lipid Abnormalities

Inform patients that hypercholesterolemia and/or hypertriglyceridemia can occur during treatment with tretinoin capsules. Advise patients on the need for monitoring fasting triglycerides and cholesterol [see Warnings and Precautions (5.6)].

Hepatotoxicity

Advise patients that tretinoin capsules can cause elevated liver function tests. Advise patients on the need for monitoring of liver function tests [see Warnings and Precautions (5.7)].

Thromboembolic Events

Inform patients that venous and arterial thromboembolic events, including cerebrovascular accident, myocardial infarction and renal infarct can occur during treatment with tretinoin capsules [see Warnings and Precautions (5.8)].

Lactation

Advise women not to breastfeed during treatment with tretinoin capsules and for 1 week after the last dose [see Use in Specific Populations (8.2)].

Administration Instructions

Advise patients to swallow tretinoin capsules whole with water. Advise patients not to chew, dissolve, or open capsules. Advise patients not to take a missed dose of tretinoin capsules unless it is more than 10 hours until the next scheduled dose. Advise patients that if vomiting occurs after tretinoin capsules administration, that they should not take an additional dose, but continue with the next scheduled dose [see Dosage and Administration (2.2)].

Effects on Ability to Drive and Use Machines

Advise patients that the ability to drive or operate machinery might be impaired when treated with tretinoin capsules, particularly if patients are experiencing dizziness or severe headache.

Trademarks are the property of their respective owners.

Manufactured by:

Douglas Manufacturing Limited

Lincoln, Auckland 0610, New Zealand

Distributed by:

Glenmark Pharmaceuticals Inc., USA

Elmwood Park, NJ 07407

Questions? 1 (888) 721-7115

www.glenmarkpharma-us.com

June 2025

PACKAGE/LABEL PRINCIPAL DISPLAY PANEL

68462-792-01

Tretinoin Capsules
10 mg

CAUSES BIRTH DEFECTS. DO NOT GET PREGNANT.